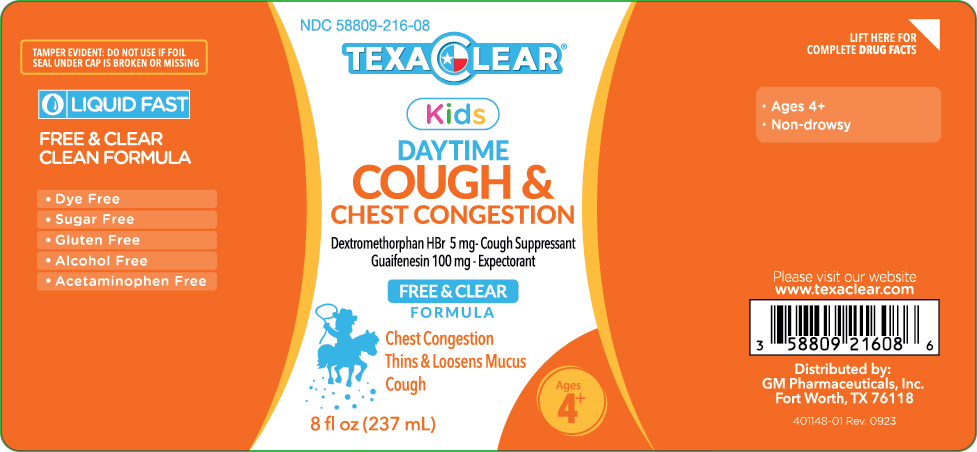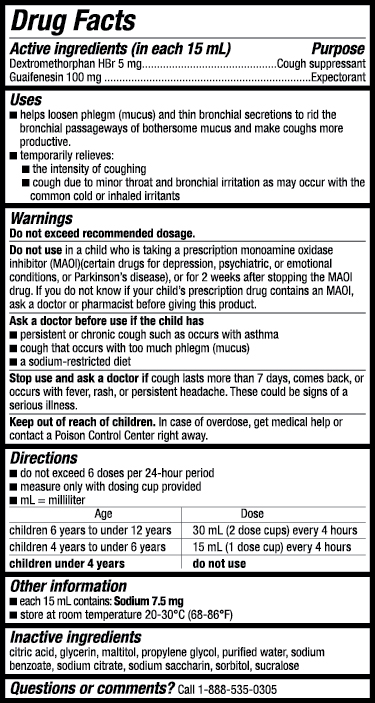 DRUG LABEL: TexaClear Kids Daytime Cough and Chest Congestion
NDC: 58809-216 | Form: LIQUID
Manufacturer: GM Pharmaceuticals, INC
Category: otc | Type: HUMAN OTC DRUG LABEL
Date: 20241007

ACTIVE INGREDIENTS: DEXTROMETHORPHAN HYDROBROMIDE 5 mg/15 mL; GUAIFENESIN 100 mg/15 mL
INACTIVE INGREDIENTS: ANHYDROUS CITRIC ACID; GLYCERIN; MALTITOL; PROPYLENE GLYCOL; WATER; SODIUM BENZOATE; SODIUM CITRATE; SACCHARIN SODIUM; SORBITOL; SUCRALOSE

TexaClear Kids Daytime Cough and Chest Congestion

TexaClear Kids Daytime Cough and Chest Congestion

(dextromethorphan HBr, guaifenesin), solution

GM Pharmaceuticals, Inc.

Drug Facts

Active ingredients (in each 15 mL)

Dextromethorphan HBr 5 mg
Guaifenesin 100 mg

Purpose

Cough suppressant
Expectorant

Uses

- helps loosen phlegm (mucus) and thin bronchial secretions to rid the bronchial passageways of bothersome mucus and make coughs more productive.
- temporarily relieves:
  - the intensity of coughing
  - cough due to minor throat and bronchial irritation as may occur with the common cold or inhaled irritants

WARNINGS

Do not exceed recommended dosage.

Do not use

in a child who is taking a prescription monoamine oxidase inhibitor (MOAI) (certain drugs for depression, pschiatric, or emotional conditions, or parkinson's disease), or for 2 weeks after stopping the MAOI drug. If you do not know if your child's prescription drug contains an MAOI, ask a doctor or pharmacist before giving this product.

Ask a doctor before use if the child has

- persistent or chronic cough such as occurs with asthma
- a cough that occurs with too much phlegm (mucus)
- a sodium-restricted diet

Stop use and ask a doctor if

cough lasts more than 7 days, comes back, or occurs with fever, rash, or persistent headache. These could be signs of a serious illness.

Keep out of reach of children.

In case of overdose, get medical help or contact a Poison Control Center right away.

Directions

- do not exceed 6 doses per 24-hour period.
- measure only with the dosing cup provided.
- mL= milliliter

Age | Dose
children 6 years to under 12 years | 30 mL (2 dose cups) every 4 hours
children 4 years to under 6 years | 15 mL (1 dose cup) every 4 hours
children under 4 years | do not use.

Other information

- each 15 mL contains: Sodium 7.5 mg
- store at room temperature 20-30°C (68-86°F)

Inactive ingredients

citric acid, glycerin, maltitol, propylene glycol, purified water, sodium benzoate, sodium citrate, sodium saccharin, sorbitol, sucralose

Questions or comments?

Call 1-888-535-0305 9 a.m. - 5 p.m. CST.

Distributed by:
GM Pharmaceuticals, Inc.
Fort Worth, TX. 76118

Principal Display Panel

TexaClear Kids Daytime Cough and Chest Congestion
NDC 58809-216-08
8 fl. oz. (237 mL)

Dextromethorphan HBR – Cough Suppressant
Guaifenesin – Expectorant

Tamper evident: do not use if foil seal under cap is broken on missing

- Dye Free
- Sugar Free
- Gluten Free
- Alcohol Free
- Acetaminophen Free

Ages 4+

Relieves:

- Chest Congestion
- Thins & Loosens Mucus
- Cough

Distributed by:
GM Pharmaceuticals, Inc. Fort Worth, TX 76118